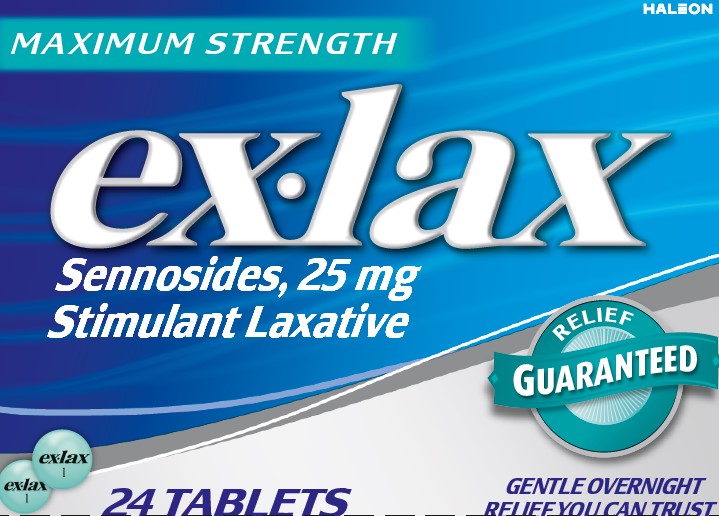 DRUG LABEL: EX-LAX
NDC: 0067-8142 | Form: PILL
Manufacturer: Haleon US Holdings LLC
Category: otc | Type: HUMAN OTC DRUG LABEL
Date: 20241217

ACTIVE INGREDIENTS: SENNOSIDES 25 mg/1 1
INACTIVE INGREDIENTS: ACACIA; CALCIUM CARBONATE; CARNAUBA WAX; STARCH, CORN; ANHYDROUS DIBASIC CALCIUM PHOSPHATE; FD&C BLUE NO. 1; ALUMINUM OXIDE; FERROSOFERRIC OXIDE; MAGNESIUM STEARATE; METHYLPARABEN; MICROCRYSTALLINE CELLULOSE; POLYETHYLENE GLYCOL 3350; POLYVINYL ALCOHOL, UNSPECIFIED; POVIDONE, UNSPECIFIED; PROPYLENE GLYCOL; PROPYLPARABEN; SHELLAC; SILICON DIOXIDE; SODIUM BENZOATE; SODIUM LAURYL SULFATE; SUCROSE; TALC; TITANIUM DIOXIDE

Drug Facts

Active ingredient (in each tablet)

Sennosides 25 mg

Purpose

Stimulant laxative

Uses

- relieves occasional constipation (irregularity)
- generally produces bowel movement in 6 to 12 hours

Warnings

Do Not Use

laxative products when abdominal pain, nausea, or vomiting are present unless directed by a doctor

Ask a doctor before use if you have

noticed a sudden change in bowel habits that persists over a period of 2 weeks

Ask a doctor or pharmacist before use if you are

taking any other drug. Laxatives may affect how other drugs work. Take this product 2 or more hours before or after other drugs.

When using this product

do not use for a period longer than 1 week

Stop use and ask a doctor if

rectal bleeding or failure to have a bowel movement occur after use of a laxative. These may be signs of a serious condition.

If pregnant or breast-feeding,

ask a health professional before use.

Keep Out of Reach of Children.

In case of overdose, get medical help or contact a Poison Control Center right away.

Directions

- swallow tablet(s) with a glass of water
- swallow tablet(s) whole, do not crush, break or chew

adults and children 12 years of age and older | 2 tablets once or twice daily
children 6 to under 12 years of age | 1 tablet once or twice daily
children under 6 years of age | ask a doctor

Other information

- each tablet contains: calcium 40 mg, magnesium 5 mg
- store at controlled room temperature 20-25C (68-77F).

Inactive ingredients

acacia, calcium carbonate, carnauba wax, corn starch dibasic calcium phosphate, FD&C blue no.1 aluminum lake, iron oxide black, magnesium stearate, methyl paraben, microcrystalline cellulose, polyethylene glycol, polyvinyl alcohol, povidone, propylene glycol, propylparaben, shellac, silicon dioxide, sodium benzoate, sodium lauryl sulfate, sucrose, talc, titanium dioxide

Questions or Comments?

call 1-855-221-5432

Additional information listed on other panels

The Ex•Lax® Guarantee: When taken as directed, Ex•Lax® is guaranteed to work gently and effectively overnight or your money back. Return product to GSK, attention Consumer Affairs, for full refund.

Tamper Evident Feature: Ex•Lax® Tablets are sealed in blister packets. Use only if the individual seal is unbroken.

Principal Display Panel

MAXIMUM STRENGTH

ex•lax

SENNOSIDES, 25 mg

STIMULANT LAXATIVE

RELIEF GUARANTEED

24 TABLETS

GENTLE OVERNIGHT RELIEF YOU CAN TRUST